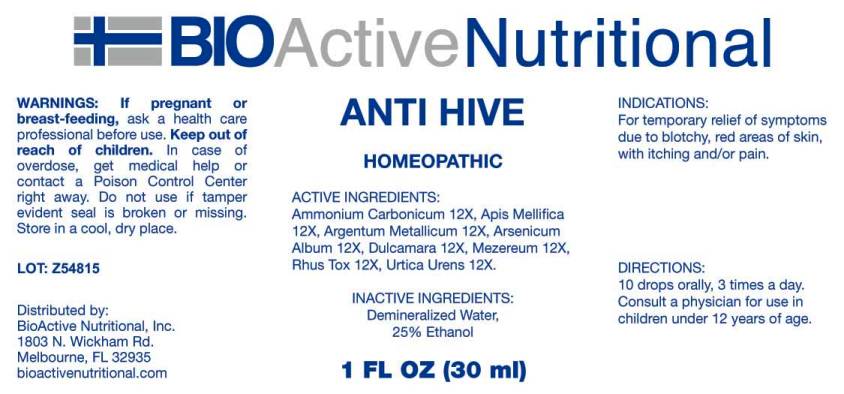 DRUG LABEL: Anti Hive
NDC: 43857-0127 | Form: LIQUID
Manufacturer: BioActive Nutritional, Inc.
Category: homeopathic | Type: HUMAN OTC DRUG LABEL
Date: 20170330

ACTIVE INGREDIENTS: AMMONIUM CARBONATE 12 [hp_X]/1 mL; APIS MELLIFERA 12 [hp_X]/1 mL; SILVER 12 [hp_X]/1 mL; ARSENIC TRIOXIDE 12 [hp_X]/1 mL; SOLANUM DULCAMARA TOP 12 [hp_X]/1 mL; DAPHNE MEZEREUM BARK 12 [hp_X]/1 mL; TOXICODENDRON PUBESCENS LEAF 12 [hp_X]/1 mL; URTICA URENS 12 [hp_X]/1 mL
INACTIVE INGREDIENTS: WATER; ALCOHOL

Drug Facts:

ACTIVE INGREDIENTS:

Ammonium Carbonicum 12X, Apis Mellifica 12X, Argentum Metallicum 12X, Arsenicum Album 12X, Dulcamara 12X, Mezereum 12X, Rhus Tox 12X, Urtica Urens 12X.

INDICATIONS:

For temporary relief of symptoms due to blotchy, red areas of skin, with itching and/or pain.

WARNINGS:

If pregnant or breast-feeding, ask a health care professional before use.

Keep out of reach of children. In case of overdose, get medical help or contact a Poison Control Center right away.

Do not use if tamper evident seal is broken or missing.

Store in cool, dry place.

DIRECTIONS:

10 drops orally, 3 times a day. Consult a physician for use in children under 12 years of age.

INACTIVE INGREDIENTS:

Demineralized Water, 25% Ethanol.

Keep out of reach of children. In case of overdose, get medical help or contact a Poison Control Center right away.

INDICATIONS:

For temporary relief of symptoms due to blotchy, red areas of skin, with itching and/or pain.

QUESTIONS:

Distributed by:
BioActive Nutritional, Inc.
1803 N. Wickham Rd.
Melbourne, FL 32935
bioactivenutritional.com

PACKAGE LABEL DISPLAY:

BIOActive Nutritional

ANTI HIVE

HOMEOPATHIC

1 FL OZ (30 ml)